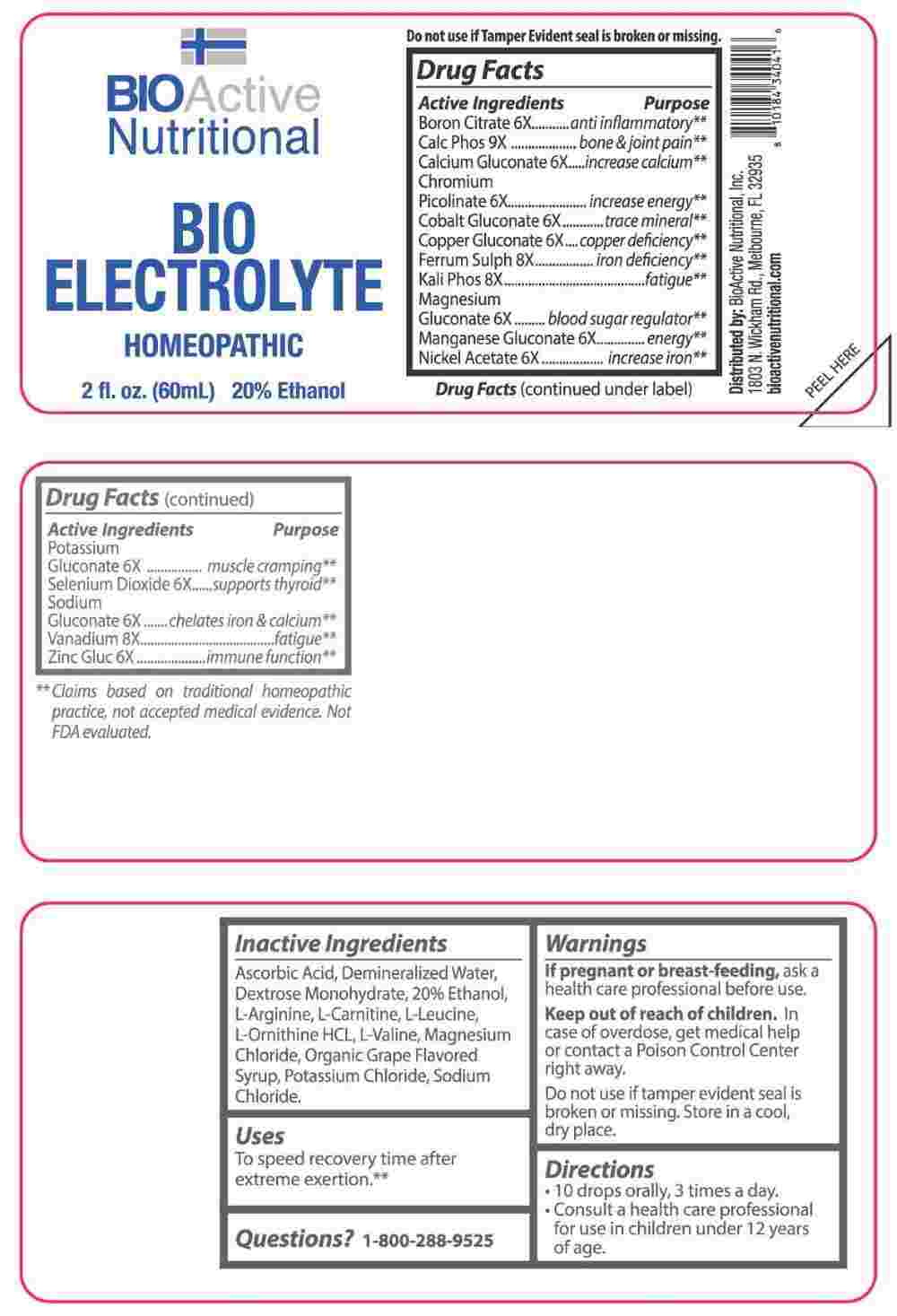 DRUG LABEL: Bio Electrolyte
NDC: 43857-0567 | Form: LIQUID
Manufacturer: BioActive Nutritional, Inc.
Category: homeopathic | Type: HUMAN OTC DRUG LABEL
Date: 20250606

ACTIVE INGREDIENTS: BORON CITRATE 6 [hp_X]/1 mL; CALCIUM GLUCONATE 6 [hp_X]/1 mL; CHROMIUM PICOLINATE 6 [hp_X]/1 mL; COBALTOUS GLUCONATE 6 [hp_X]/1 mL; COPPER GLUCONATE 6 [hp_X]/1 mL; MAGNESIUM GLUCONATE 6 [hp_X]/1 mL; MANGANESE GLUCONATE 6 [hp_X]/1 mL; NICKEL ACETATE 6 [hp_X]/1 mL; POTASSIUM GLUCONATE 6 [hp_X]/1 mL; SELENIUM DIOXIDE 6 [hp_X]/1 mL; SODIUM GLUCONATE 6 [hp_X]/1 mL; ZINC GLUCONATE 6 [hp_X]/1 mL; FERROUS SULFATE 8 [hp_X]/1 mL; DIBASIC POTASSIUM PHOSPHATE 8 [hp_X]/1 mL; VANADIUM 8 [hp_X]/1 mL; TRIBASIC CALCIUM PHOSPHATE 9 [hp_X]/1 mL
INACTIVE INGREDIENTS: ASCORBIC ACID; DEXTROSE MONOHYDRATE; ALCOHOL; ARGININE; LEVOCARNITINE; LEUCINE; ORNITHINE HYDROCHLORIDE; VALINE; MAGNESIUM CHLORIDE; WATER; WINE GRAPE JUICE; POTASSIUM CHLORIDE; SODIUM CHLORIDE

Drug Facts:

ACTIVE INGREDIENTS:

Boron Citrate 6X, Calcarea Phosphorica 9X, Calcium Gluconate 6X, Chromium Picolinate 6X, Cobalt Gluconate 6X, Copper Gluconate 6X, Ferrum Sulphuricum 8X, Kali Phosphoricum 8X, Magnesium Gluconicum Dihydricum 6X, Manganese Gluconate 6X, Nickel Acetate 6X, Potassium Gluconate 6X, Selenium Dioxide 6X, Sodium Gluconate 6X, Vanadium Metallicum 8X, Zincum Gluconicum 6X.

PURPOSE:

Boron Citrate – anti inflammatory,** Calcarea Phosphorica – bone & joint pain,** Calcium Gluconate – increase calcium,** Chromium Picolinate – increase energy,** Cobalt Gluconate – trace mineral, **Copper Gluconate – copper deficiency,** Ferrum Sulphuricum – iron deficiency,** Kali Phosphoricum - fatigue,** Magnesium Gluconicum Dihydricum – blood sugar regulator,** Manganese Gluconate - energy,** Nickel Acetate – increase iron,** Potassium Gluconate – muscle cramping,** Selenium Dioxide – supports thyroid,** Sodium Gluconate – chelates iron & calcium,** Vanadium Metallicum - fatigue,** Zincum Gluconicum – immune function**

**Claims based on traditional homeopathic practice, not accepted medical evidence. Not FDA evaluated.

USES:

To speed recovery time after extreme exertion.**

**Claims based on traditional homeopathic practice, not accepted medical evidence. Not FDA evaluated.

WARNINGS:

If pregnant or breast-feeding, ask a health care professional before use.

Keep out of reach of children. In case of overdose, get medical help or contact a Poison Control Center right away.

Do not use if tamper evident seal is broken or missing.

Store in a cool, dry place.

KEEP OUT OF REACH OF CHILDREN:

In case of overdose, get medical help or contact a Poison Control Center right away.

DIRECTIONS:

• 10 drops orally, 3 times a day.

• Consult a health care professional for use in children under 12 years of age.

INACTIVE INGREDIENTS:

Ascorbic Acid, Demineralized Water, Dextrose Monohydrate, 20% Ethanol, L-Arginine, L-Carnitine, L-Leucine, L-Ornithine HCL, L-Valine, Magnesium Chloride, Organic Grape Flavored Syrup, Potassium Chloride, Sodium Chloride.

QUESTIONS:

Distributed by:
BioActive Nutritional, Inc.
1803 N. Wickham Rd.
Melbourne, FL 32935
bioactivenutritional.com

1-800-288-95-25

PACKAGE LABEL DISPLAY:

BIOActive Nutritional

BIO ELECTROLYTE

HOMEOPATHIC

2 fl. oz. (60mL)